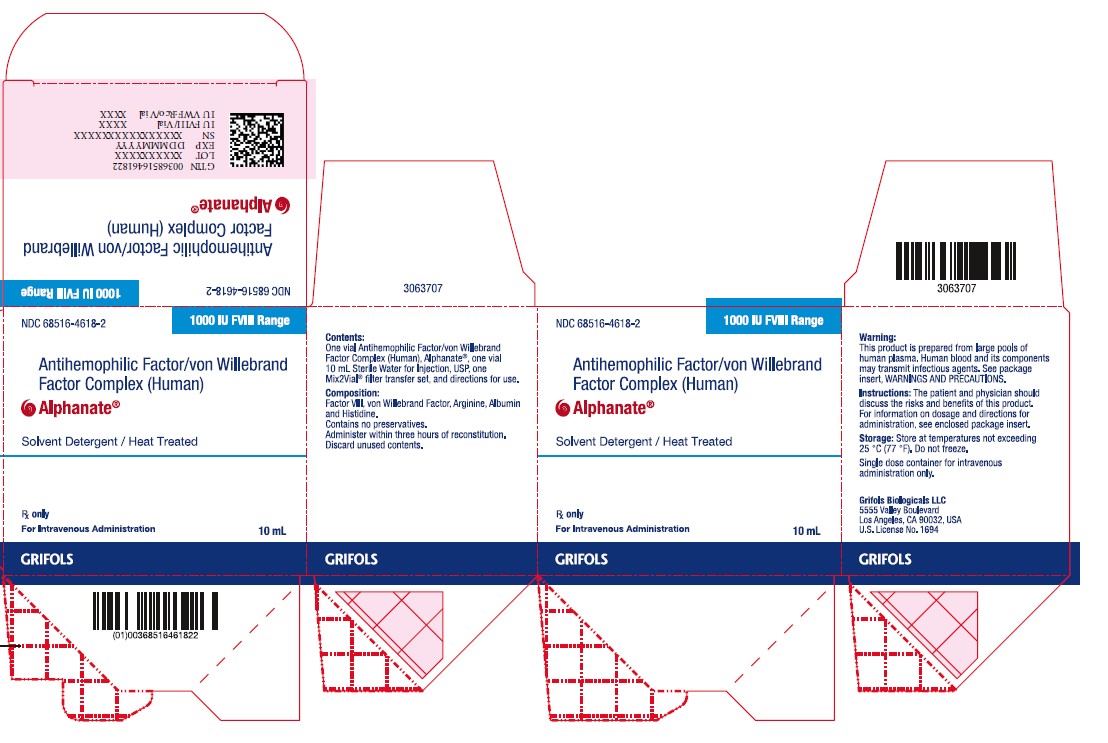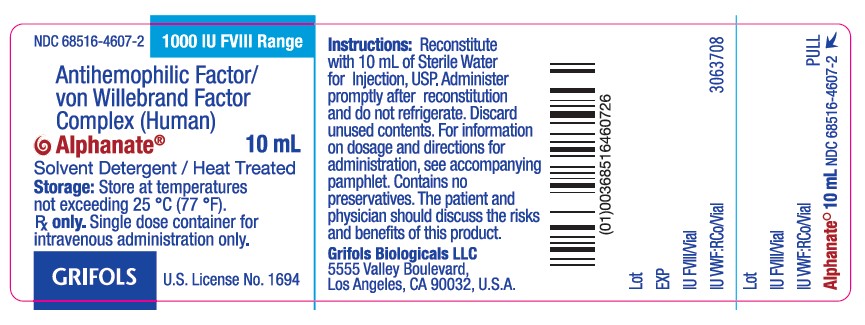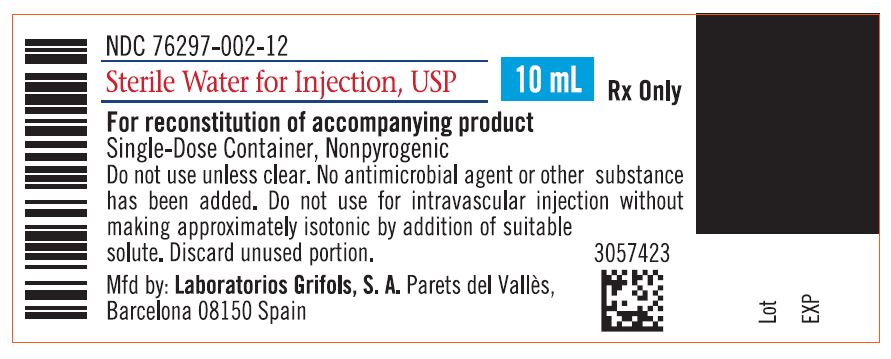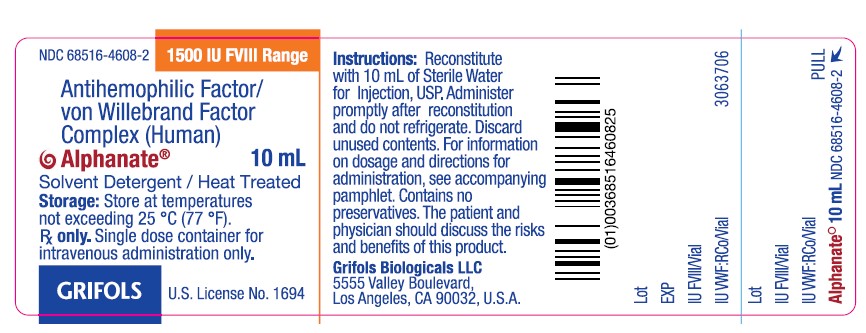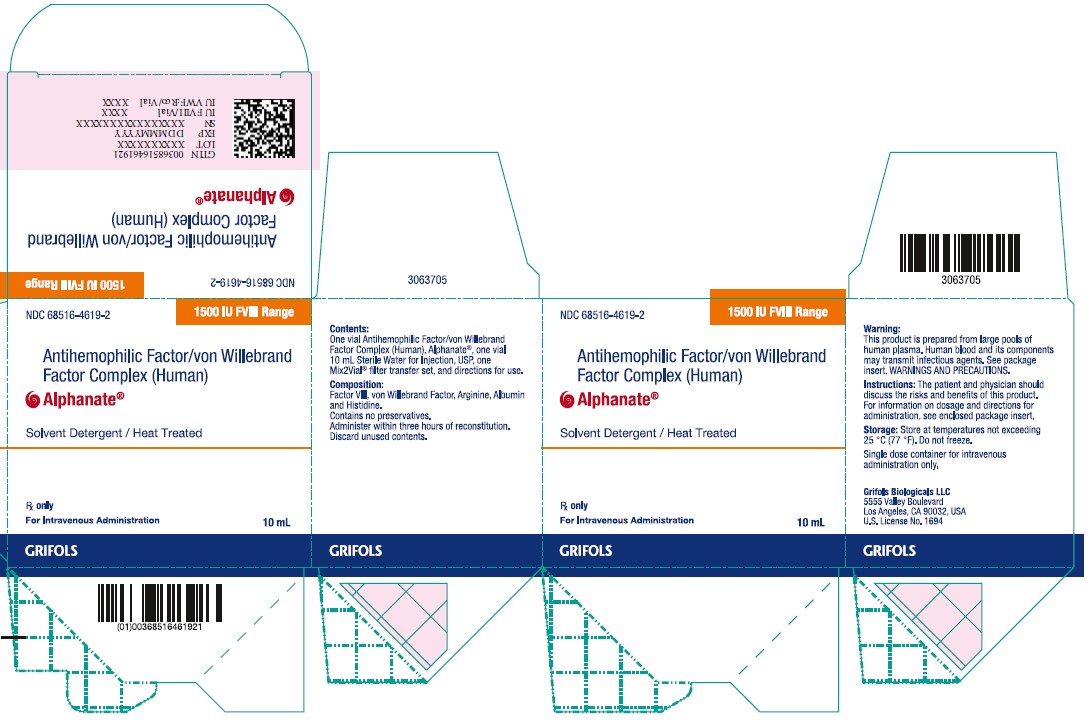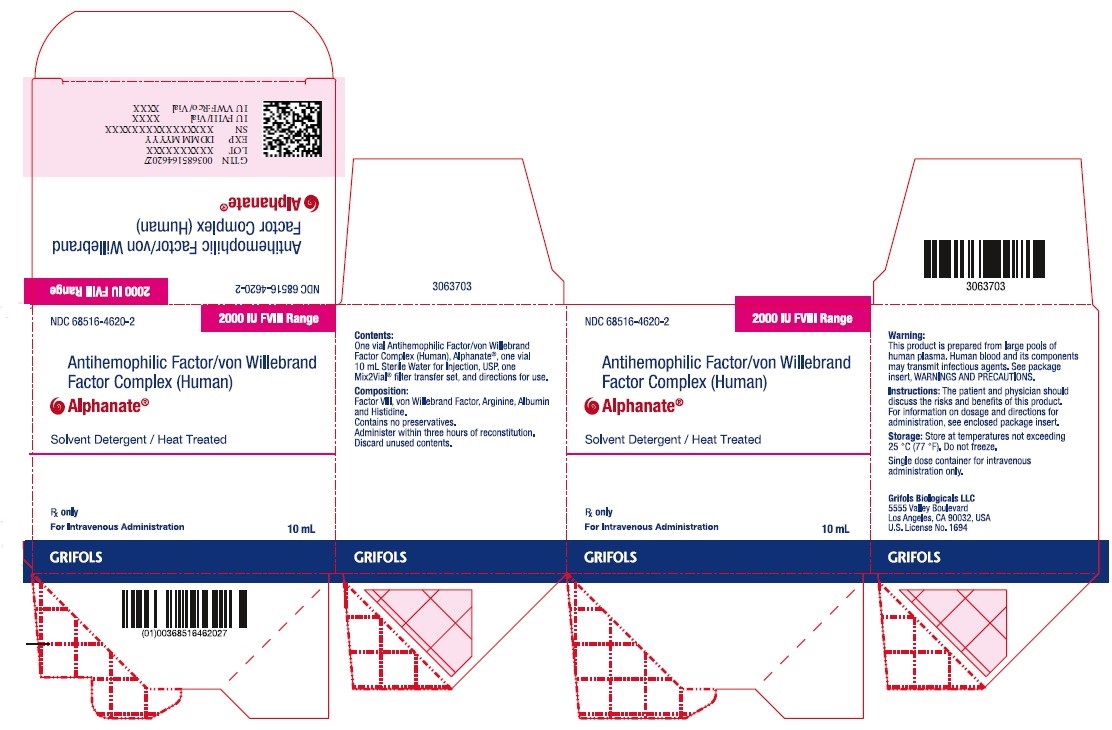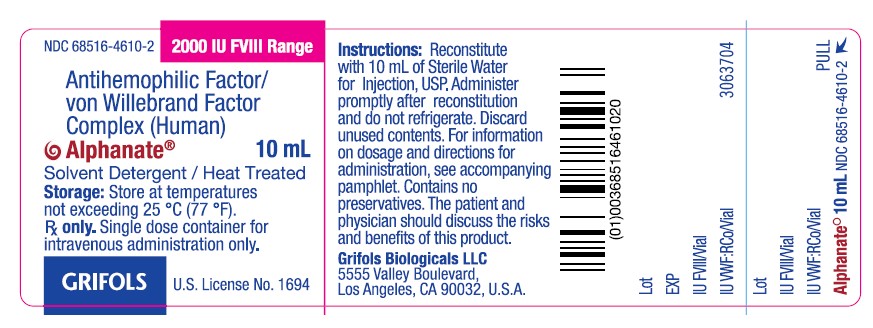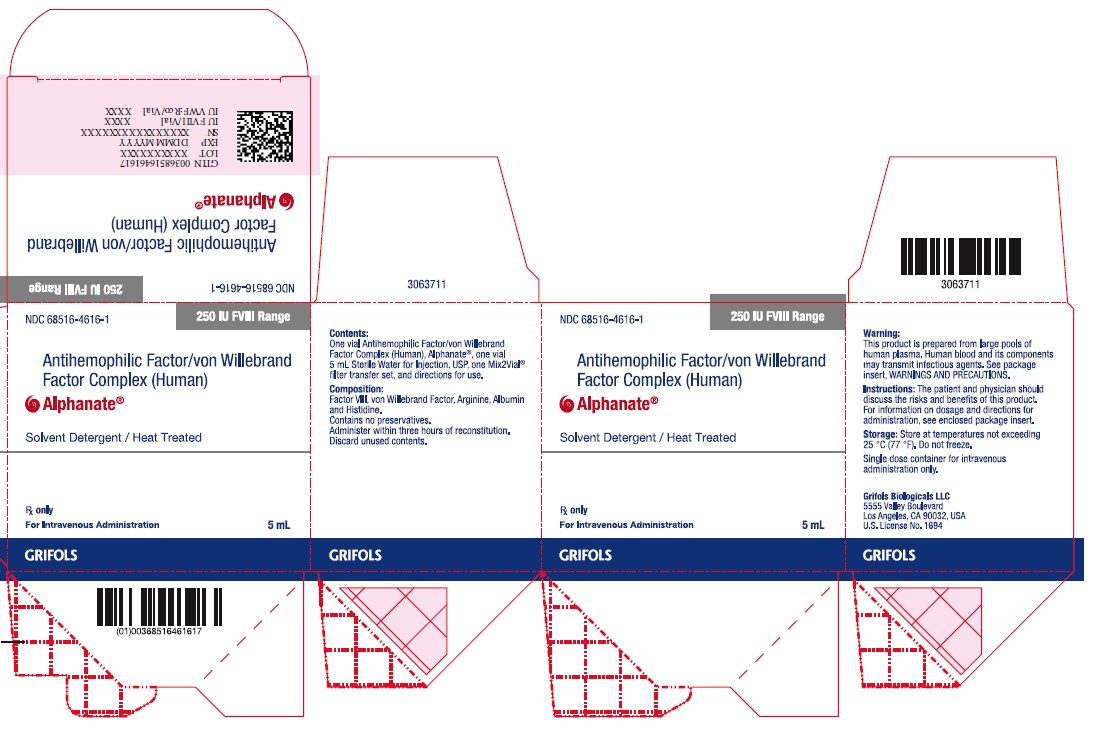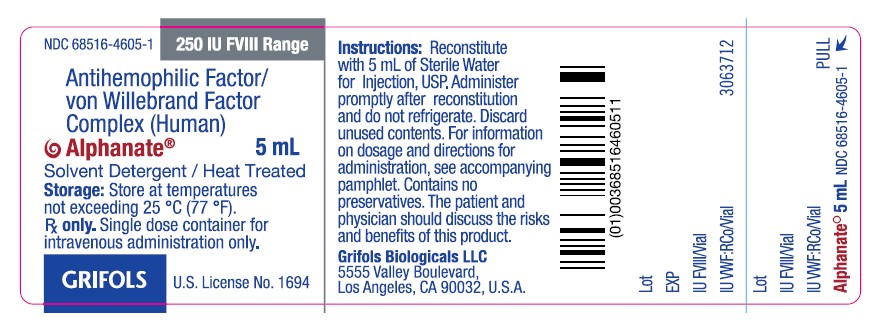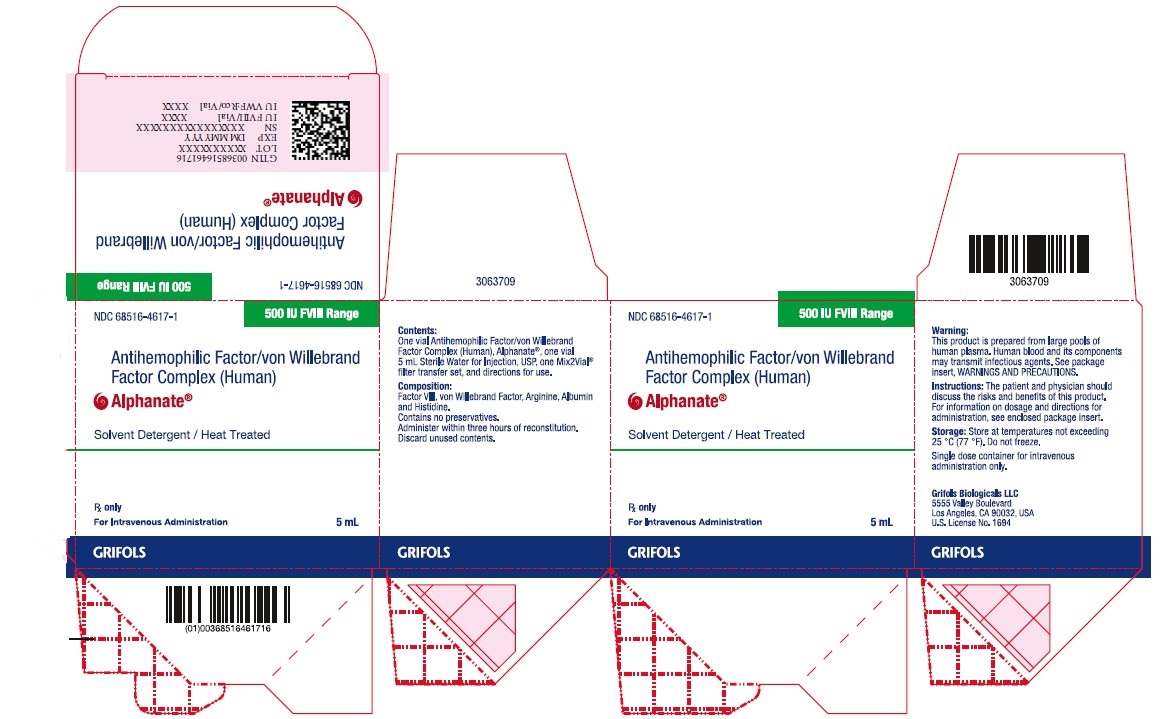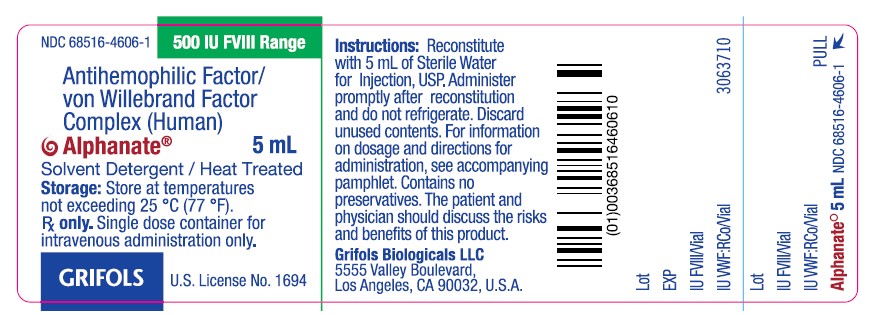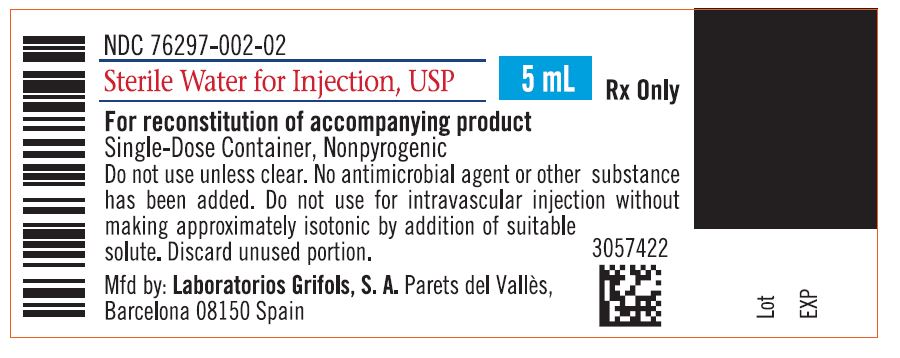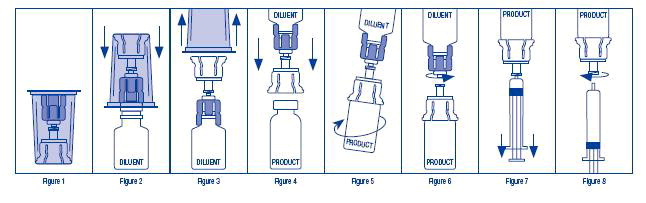 DRUG LABEL: Alphanate
NDC: 68516-4611 | Form: KIT | Route: INTRAVENOUS
Manufacturer: GRIFOLS USA, LLC
Category: other | Type: PLASMA DERIVATIVE
Date: 20250522

ACTIVE INGREDIENTS: HUMAN COAGULATION FACTOR VIII/VON WILLEBRAND FACTOR COMPLEX 250 [iU]/5 mL; water 1 mL/1 mL
INACTIVE INGREDIENTS: Albumin Human; arginine; histidine

HIGHLIGHTS OF PRESCRIBING INFORMATION

These highlights do not include all the information needed to use ALPHANATE safely and effectively. See full prescribing information for ALPHANATE.
ALPHANATE (ANTIHEMOPHILIC FACTOR/VON WILLEBRAND FACTOR COMPLEX [HUMAN])
Lyophilized Powder for Solution for Intravenous Injection
Initial U.S. Approval: 1978

1 INDICATIONS AND USAGE

ALPHANATE, (antihemophilic factor/von Willebrand factor complex [human]), is indicated for:

- Control and prevention of bleeding in adult and pediatric patients with hemophilia A.
- Surgical and/or invasive procedures in adult and pediatric patients with von Willebrand Disease in whom desmopressin (DDAVP) is either ineffective or contraindicated. It is not indicated for patients with severe VWD (Type 3) undergoing major surgery.

2 DOSAGE AND ADMINISTRATION

For intravenous injection after reconstitution only.

ALPHANATE contains the labeled amount of factor VIII expressed in International Units (IU) FVIII/vial and von Willebrand Factor:Ristocetin Cofactor activity in IU VWF:RCo/vial (2).

Dose (2.1)

Treatment and Prevention of Bleeding Episodes and Excess Bleeding During and After Surgery in Patients with Hemophilia A

- Dose (units) = body weight (kg) x desired FVIII rise (IU/dL or % of normal) x 0.5 (IU/kg per IU/dL).
- Dosing frequency determined by the type of bleeding episode and the recommendation of the treating physician.

Treatment and Prevention of Excess Bleeding During and After Surgery or Other Invasive Procedures in Patients with von Willebrand Disease

- Adults: Pre-operative dose of 60 IU VWF:RCo/kg body weight; subsequent doses of 40-60 IU VWF:RCo/kg body weight.
- Pediatric: Pre-operative dose of 75 IU VWF:RCo/kg body weight; subsequent doses of 50-75 IU VWF:RCo/kg body weight.

3 DOSAGE FORMS AND STRENGTHS

ALPHANATE is available as a lyophilized powder for intravenous injection after reconstitution in single dose vials containing 250, 500, 1000, 1500 and 2000 IU FVIII (3).

4 CONTRAINDICATIONS

Do not use in patients who have manifested life-threatening immediate hypersensitivity reactions, including anaphylaxis, to the product or its components (4).

5 WARNINGS AND PRECAUTIONS

- Anaphylaxis and severe hypersensitivity reactions are possible. Discontinue treatment with ALPHANATE and administer appropriate emergency treatment should symptoms of anaphylaxis or severe hypersensitivity occur (5.1).
- Development of activity-neutralizing antibodies may occur in patients receiving FVIII containing products (5.2).
- Thromboembolic events (TE) may occur in VWD patients, especially with known risk factors. Monitor patients for signs and symptoms of TE (5.3).
- Intravascular hemolysis may occur with infusion of large doses of Antihemophilic Factor/von Willebrand Factor Complex. Should this condition occur and lead to progressive hemolytic anemia, discontinue administration of ALPHANATE and consider alternative therapy (5.4).
- Rapid administration may result in vasomotor reactions (5.5).
- ALPHANATE is made from human plasma and may carry a risk of transmitting infectious agents, e.g., viruses, the variant Creutzfeldt-Jakob disease (vCJD) agent and theoretically, the Creutzfeldt-Jakob disease (CJD) agent (5.6).
- Perform assays to determine if FVIII inhibitors are present (5.7).

6 ADVERSE REACTIONS

The most frequent adverse drug reactions reported with ALPHANATE in >1% of infusions were pruritus, headache, back pain, paresthesia, respiratory distress, facial edema, pain, rash and chills (6).

To report SUSPECTED ADVERSE REACTIONS, contact Grifols Biologicals LLC at 1-888-GRIFOLS (1-888-474-3657) or FDA at 1-800-FDA-1088 www.fda.gov/medwatch

8 USE IN SPECIFIC POPULATIONS

- Pregnancy: No human or animal data. Use only if clearly needed (8.1).
- Pediatric: Age had no effect on the pharmacokinetics of ALPHANATE (8.4).

FULL PRESCRIBING INFORMATION

1 INDICATIONS AND USAGE

ALPHANATE, (antihemophilic factor/von Willebrand factor complex [human]), is indicated for:

- Control and prevention of bleeding episodes and perioperative management in adult and pediatric patients with Factor VIII (FVIII) deficiency due to hemophilia A.
- Surgical and/or invasive procedures in adult and pediatric patients with von Willebrand Disease (VWD) in whom desmopressin (DDAVP) is either ineffective or contraindicated. It is not indicated for patients with severe VWD (Type 3) undergoing major surgery.

2 DOSAGE AND ADMINISTRATION

For intravenous injection after reconstitution only

- Treatment with ALPHANATE should be initiated under the supervision of a physician experienced in the treatment of hemophilia.
- Each vial of ALPHANATE has the antihemophilic factor (AHF) potency (FVIII:C activity) expressed in International Units (IU) FVIII/vial on the label. Additionally, ALPHANATE contains von Willebrand Factor:Ristocetin Cofactor (VWF:RCo), which is expressed in IU VWF:RCo/vial for the treatment of VWD.

2.1 Dose

Treatment and Prevention of Bleeding Episodes and Excess Bleeding During and After Surgery in Patients with Hemophilia A

- Dosage and duration of treatment depend on the severity of the FVIII deficiency, the location and extent of bleeding, presence of inhibitors, and the patient’s clinical condition. Careful control of replacement therapy is especially important in cases of major surgery or life-threatening bleeding episodes.
- Dosing requirements and frequency of dosing is calculated on the basis of an expected initial response of 2% of normal FVIII:C increase per IU FVIII:C/kg body weight administered.^1The expected in vivo peak increase in FVIII level expressed as IU/dL (or % of normal) can be estimated using the following formulas:

Dosage (international units) = body weight (kg) x desired FVIII rise (IU/dL or % normal) x 0.5 (IU/kg per IU/dL)

or

IU/dL (or % of normal) = [Total Dose (IU)/body weight (kg)] x 2

- Titrate dose and frequency to the patient’s clinical response, including individualized needs, severity of the deficiency, severity of the hemorrhage, presence of inhibitors, and FVIII level desired. Patients may vary in their pharmacokinetic (e.g., half-life, in vivo recovery) and clinical responses to ALPHANATE.
- Table 1 provides dosage guidelines for the control and prevention of bleeding episodes in hemophilia A patients. Dosing should aim at maintaining a plasma factor VIII activity level at or above the plasma levels (in IU/dL or in % of normal) outlined in the table.

Table 1: Dosage Guidelines for Patients with Hemophilia A
Type of Bleeding | FVIII:C Level Required (% of normal) | Doses (IU/kg) | Frequency of Doses (hours) | Duration of Therapy (days)
Minor • Large bruises • Significant cuts or scrapes • Uncomplicated joint hemorrhage | 30 | 15 | 12 (twice daily) | Until hemorrhage stops and healing has been achieved (1–2 days).
Moderate • Nose, mouth and gum bleeds • Dental extractions Hematuria | 50 | 25 | 12 (twice daily) | Until healing has been achieved (2–7 days, on average).
Major • Joint hemorrhage • Muscle hemorrhage • Major trauma • Hematuria • Intracranial and intraperitoneal bleeding | 80–100 | Initial: 40–50 Maintenance: 25 | 12 (twice daily) | For at least 3–5 days Until healing has been achieved for up to 10 days. Intracranial hemorrhage may require prophylaxis therapy for up to 6 months.
Surgery | Prior to surgery: 80–100 After surgery: 60–100 | 40–50 30–50 | Once 12 (twice daily) | Prior to surgery For the next 7–10 days, or until healing has been achieved.

- Monitoring parameters:
  - Monitor plasma FVIII levels periodically to evaluate individual patient response to the dosage regimen.
  - If dosing studies have determined that a particular patient exhibits a lower/higher than expected response and shorter/longer half-life, adjust the dose and the frequency of dosing accordingly.
  - Failure to achieve the expected plasma FVIII:C level or to control bleeding after an appropriately calculated dosage may be indicative of the development of an inhibitor (an antibody to FVIII:C). Quantitate the inhibitor level by appropriate laboratory procedures and document its presence. Treatment with AHF in such cases must be individualized.^2

Treatment and Prevention of Excess Bleeding During and After Surgery or Other Invasive Procedures in Patients with von Willebrand Disease

- The ratio of VWF:RCo to FVIII in ALPHANATE varies by lot, so with each new lot, check IU VWF:RCo/vial to ensure accurate dosing.
- Dosage and duration of treatment depend on the severity of the VWF deficiency, the location and extent of bleeding, and the patient’s clinical condition. Careful control of replacement therapy is especially important in cases of major surgery or life-threatening bleeding episodes.
- The median incremental in vivo recoveries of VWF:RCo and FVIII:C were 3.12 (IU/dL)/(IU/kg) [mean, 3.29 ± 1.46 (IU/dL)/(IU/kg); range: 1.28 to 5.73 (IU/dL)/(IU/kg)] for VWF:RCo and 1.95 (IU/dL)/(IU/kg) [mean, 2.13 ± 0.58 (IU/dL)/(IU/kg); range: 1.33 to 3.32 (IU/dL)/(IU/kg)] for FVIII:C.
- Table 2 provides dosing guidelines for pediatric and adult patients with von Willebrand Disease.^3-6

Table 2: Dosage Guidelines for Patients with von Willebrand Disease (Except Type 3 Subjects Undergoing Major Surgery)
Minor Surgery/Bleeding
Parameter | VWF:RCo | Target FVIII:C Activity Levels
Pre-operative/pre-procedure dose: | Adults: 60 IU VWF:RCo/kg body weight. Pediatrics: 75 IU VWF:RCo/kg body weight. | 40-50 IU/dL
Maintenance dose: | Adults: 40 to 60 IU VWF:RCo/kg body weight at 8 to 12 hour intervals as clinically needed for 1-3 days. Pediatrics: 50 to 75 IU VWF:RCo/kg body weight at 8 to 12 hour intervals as clinically needed for 1-3 days. | 40-50 IU/dL
Therapeutic Goal (Trough)a : | >50 IU/dL | >50 IU/dL
Safety Monitoring: | Peak and trough at least once daily | Peak and trough at least once daily
Safety Parameterb : | Should not exceed 150 IU/dL | Should not exceed 150 IU/dL
Major Surgery/Bleeding
Parameter | VWF:RCo | Target FVIII:C Activity Levels
Pre-operative/pre-procedure dose: | Adults: 60 IU VWF:RCo/kg body weight. Pediatrics: 75 IU VWF:RCo/kg body weight. | 100 IU/dL
Maintenance dose: | Adults: 40 to 60 IU VWF:RCo/kg body weight at 8 to 12 hour intervals as clinically needed for at least 3-7 days. Pediatrics: 50 to 75 IU VWF:RCo/kg body weight at 8 to 12 hour intervals as clinically needed for at least 3-7 days. | 100 IU/dL
Therapeutic Goal (Trough)a : | >50 IU/dL | >50 IU/dL
Safety Monitoring: | Peak and trough at least daily | Peak and trough at least daily
Safety Parameterb: | Should not exceed 150 IU/dL | Should not exceed 150 IU/dL
a The therapeutic goal is referenced in the NHLBI Guidelines.^7
b The safety parameter is extracted from Mannucci 2009.^8

2.2 Reconstitution

1. Always use aseptic technique.
2. Ensure that concentrate (ALPHANATE) and diluent (Sterile Water for Injection, USP) are at room temperature (but not above 37 ˚C) before reconstitution.
3. Remove the plastic flip off cap from the diluent vial.
4. Gently swab the exposed stopper surface with a cleansing agent such as alcohol trying to avoid leaving any excess cleansing agent on the stopper.
5. Open the Mix2Vial package by peeling away the lid (Figure 1). Leave the Mix2Vial in the clear outer packaging.
6. Place the diluent vial upright on an even surface and hold the vial tight and pick up the Mix2Vial in its clear outer packaging. Holding the diluent vial securely, push the blue end of the Mix2Vial vertically down through the diluent vial stopper (Figure 2).
7. While holding onto the diluent vial, carefully remove the clear outer packaging from the Mix2Vial set, ensuring the Mix2Vial remains attached to the diluent vial (Figure 3).
8. Place the product vial upright on an even surface, invert the diluent vial with the Mix2Vial attached.
9. While holding the product vial securely on a flat surface, push the clear end of the Mix2Vial set vertically down through the product vial stopper (Figure 4). The diluent will automatically transfer out of its vial into the product vial.
  NOTE: If the Mix2Vial is connected at an angle, the vacuum may be released from the product vial and the diluent will not transfer into the product vial.
10. With the diluent and product vials still attached to the Mix2Vial, gently swirl the product vial to ensure the product is fully dissolved (Figure 5). Reconstitution requires less than 5 minutes. Do not shake the vial.
11. Disconnect the Mix2Vial into two separate pieces (Figure 6) by holding each vial adapter and twisting counterclockwise. After separating, discard the diluent vial with the blue end of the Mix2Vial.
12. Draw air into an empty, sterile syringe. Keeping the product vial upright with the clear end of the Mix2Vial attached, screw the disposable syringe onto the luer lock portion of the Mix2Vial device by pressing and twisting clockwise. Inject air into the product vial.
13. While keeping the syringe plunger depressed, invert the system upside down and draw the reconstituted product into the syringe by pulling the plunger back slowly (Figure 7).
14. When the reconstituted product has been transferred into the syringe, firmly hold the barrel of the syringe and the clear vial adapter (keeping the syringe plunger facing down) and unscrew the syringe from the Mix2Vial (Figure 8). Hold the syringe upright and push the plunger until no air is left in the syringe. Attach the syringe to a venipuncture set.
  NOTE: If the same patient is to receive more than one vial of concentrate, the contents of two vials may be drawn into the same syringe through a separate unused Mix2Vial set before attaching to the venipuncture set.
15. When reconstitution procedure is strictly followed, a few small particles may occasionally remain. The Mix2Vial set will remove particles and the labeled potency will not be reduced.
16. Discard all reconstitution equipment after use into the appropriate safety container. Do not reuse.
17. Use the prepared drug as soon as possible within 3 hours after reconstitution.

2.3 Administration

For intravenous use after reconstitution only

- Inspect parenteral drug products visually for particulate matter and discoloration prior to administration, whenever solution and container permit.
- Do not refrigerate after reconstitution. Store reconstituted ALPHANATE at room temperature (not to exceed 30 °C) prior to administration, but administer intravenously within three hours.
- Use plastic disposable syringes.
- Do not administer ALPHANATE at a rate exceeding 10 mL/minute.
- Discard any unused contents into the appropriate safety container.

3 DOSAGE FORMS AND STRENGTHS

ALPHANATE is available as a lyophilized powder for intravenous injection after reconstitution. It is available in the following potencies:

250 IU FVIII/5 mL single dose vial
500 IU FVIII/5 mL single dose vial
1000 IU FVIII/10 mL single dose vial
1500 IU FVIII/10 mL single dose vial
2000 IU FVIII/10 mL single dose vial

4 CONTRAINDICATIONS

ALPHANATE is contraindicated in patients who have manifested life-threatening immediate hypersensitivity reactions, including anaphylaxis, to the product or its components [see Adverse Reactions (6)].

5 WARNINGS AND PRECAUTIONS

5.1 Hypersensitivity Reactions

Anaphylaxis and severe hypersensitivity reactions are possible with ALPHANATE. Early signs of allergic reactions, which can progress to anaphylaxis, may include angioedema, chest tightness, hypotension, rash, nausea, vomiting, paresthesia, restlessness, wheezing and dyspnea. Discontinue use of ALPHANATE if hypersensitivity symptoms occur, and initiate appropriate treatment.

5.2 Neutralizing Antibodies

Development of procoagulant activity-neutralizing antibodies (inhibitors) has been detected in patients receiving FVIII-containing products. Carefully monitor patients treated with AHF products for the development of FVIII inhibitors by appropriate clinical observations and laboratory tests. No specific studies have been conducted with ALPHANATE to evaluate inhibitor formation. If expected plasma FVIII activity levels are not attained, or if bleeding is not controlled with an appropriate dose, perform an appropriate assay that measures FVIII inhibitor concentration.

5.3 Thromboembolic Events

Thromboembolic events have been reported in von Willebrand Disease patients receiving replacement therapy with Antihemophilic Factor/von Willebrand Factor Complexes, especially in those with known risk factors for thrombosis including but not limited to elderly age, previous thrombosis, metabolic syndrome, cancer, surgery, oral contraceptive and hormone therapy, diabetes, hypertension, hyperlipidemia, smoking, and pregnancy.^9 Monitor plasma levels of VWF:RCo and FVIII activities to avoid sustained excessive VWF and FVIII activity levels (greater than 150 IU/dL), which may increase the risk of thrombotic events, during continued treatment of replacement therapy with Antihemophilic Factor/von Willebrand Factor Complexes. Consider antithrombotic measures in VWD patients at risk for thrombosis [see Adverse Reactions (6)].

5.4 Intravascular Hemolysis

ALPHANATE contains blood group specific isoagglutinins. Monitor the patient for signs of intravascular hemolysis and decreasing hematocrit when large and/or frequent doses of Antihemophilic Factor/von Willebrand Factor Complexes are required in patients of blood groups A, B, or AB, as cases of acute hemolytic anemia, increased bleeding tendency or hyperfibrinogenemia have been reported. These events typically subside after cessation of the factor concentrate infusion.^10 Consider alternative therapy should this condition worsen despite discontinuation of ALPHANATE.

5.5 Vasomotor Reactions

Rapid administration of a FVIII concentrate may result in vasomotor reactions. Do not administer ALPHANATE at a rate exceeding 10 mL/minute.

5.6 Transmissible Infectious Agents

Because ALPHANATE is made from human plasma, it may carry a risk of transmitting infectious agents, e.g., viruses, the variant Creutzfeldt-Jakob Disease (vCJD) agent and theoretically, the Creutzfeldt-Jakob disease (CJD) agent. The risk that such products will transmit an infectious agent has been reduced by screening plasma donors for prior exposure to certain viruses, by testing for the presence of certain virus infections, and by inactivating and/or removing certain viruses during manufacturing. [see Description (11)].

5.7 Monitoring Laboratory Tests

Monitor for development of FVIII and VWF inhibitors. Perform appropriate assays to determine if FVIII and/or VWF inhibitor(s) are present if bleeding is not controlled with expected dose of ALPHANATE.

Monitor plasma levels of VWF:RCo and FVIII activities to avoid sustained excessive VWF and FVIII activity levels (greater than 150 IU/dL), which may increase the risk of thrombotic events, particularly in patients with known risk factors.

6 ADVERSE REACTIONS

Serious adverse drug reactions (ADRs) observed in patients receiving ALPHANATE include anaphylaxis/hypersensitivity reactions. Thromboembolic events also have been observed in patients receiving ALPHANATE for VWD [see Warnings and Precautions (5.3)].

6.1 Clinical Trial Experience

Because clinical trials are conducted under widely varying conditions, adverse drug reaction (ADR) rates observed in the clinical trials of a drug cannot be directly compared to rates in clinical trials of another drug and may not reflect the rates observed in clinical practice.

Hemophilia A

In a prospective clinical study with ALPHANATE, 23 subjects were exposed to 1217 infusions (median=42, range 2-160). The total number of exposure days was 1133, and the total number of months on study across all subjects was 234 (19.5 subject years). No ADRs or inhibitors to FVIII were reported during the study.

von Willebrand Disease

In the prospective clinical study of ALPHANATE[using both ALPHANATE Solvent Detergent (A-SD, a previous generation product) and ALPHANATE Solvent Detergent/Heat Treated (A-SD/HT, the current generation product)] in subjects with von Willebrand Disease, ADRs occurred in 5 of 36 subjects (13.9%) treated with ALPHANATE.

Sixty-one total ADRs were reported in 204 infusions. The majority of ADRs were rated as mild (55 of 61 [90.2%]). Six ADRs (9.8%) were rated as moderate. No reactions rated as serious were reported. The adverse drug reaction grading scale is defined as follows:

- Mild: the event was noted but the administration of the compound was not interrupted; the event resolved spontaneously or no treatment was required beyond administration of nonprescription analgesics.
- Moderate: the administration of the compound was not necessarily interrupted; the event required momentary treatment with prescription drugs and produced no sequelae.

Overall, the proportion of infusions associated with ADRs was 14 of 204 infusions (6.9%).

The most common ADRs reported (> 1% of infusions) were pruritus, headache, backpain, paresthesia, respiratory distress, facial edema, pain, rash, and chills.

One incident of pulmonary embolism was reported that was considered to have a possible relationship to the product. This subject received a dose of 60 IU VWF:RCo/kg body weight and the FVIII:C level achieved was 290%.

In the retrospective study conducted to determine the efficacy and safety of ALPHANATE (A-SD/HT) in a surgical or invasive procedure setting as perioperative prophylaxis against excessive bleeding, [see Clinical Studies (14)], 3 out of 39 subjects (7.7%) experienced 6 adverse drug reactions. Four were considered mild and 2 were considered moderate. No subject discontinued their treatment due to an adverse drug reaction. The adverse drug reactions were pruritus, paresthesia (2 events) and hemorrhage (all considered mild), and one event each of moderate hematocrit decrease and orthostatic hypotension.

One adverse drug reaction (pain) related to the treatment with heat-treated ALPHANATE (A-SD/HT) was reported in the four pediatric subjects with von Willebrand Disease during the course of the prospective study and in none of the five pediatric subjects in the retrospective clinical study.

6.2 Post-Marketing Experience

Because these reactions are reported voluntarily from a population of uncertain size, it is not always possible to reliably estimate their frequency or establish a causal relationship to drug exposure.

The most common post-marketing ADRs reported include allergic/hypersensitivity reactions, nausea, fever, joint pain, fatigue, and infusion site pain.

8 USE IN SPECIFIC POPULATIONS

8.1 Pregnancy

Pregnancy Category C. Animal reproduction studies have not been conducted with ALPHANATE. It is also not known whether ALPHANATE can cause fetal harm when administered to a pregnant woman or affect reproductive capacity. ALPHANATE should be given to a pregnant woman only if clearly needed.

8.2 Labor and Delivery

No human or animal data. Use only if clearly needed.

8.3 Nursing Mothers

No human or animal data. Use only if clearly needed.

8.4 Pediatric Use

Hemophilia A

A total of 21 children (ages 7-16) were included in clinical trials with ALPHANATE. Subjects received ALPHANATE weekly for prophylaxis or suspected bleeds. They were successfully treated for 1499 bleeding episodes or as prophylaxis to prevent them (e.g. pain in the joint). The median number of units needed to treat the bleeds was 420 IU, with a range of 210 to 1620 IU. Adult and pediatric subjects did not differ in their response to treatment.

Von Willebrand Disease

The hemostatic efficacy of ALPHANATE has been studied in 20 pediatric subjects (ages 7-18) with VWD. Based on the data from a subset of these subjects, age had no effect on the pharmacokinetics of VWF:RCo. Adult and pediatric subjects did not differ in their response to treatment.

8.5 Geriatric Use

No human or animal data. Use only if clearly needed.

11 DESCRIPTION

ALPHANATE, (antihemophilic factor/von Willebrand factor complex [human]), is a sterile, lyophilized concentrate of FVIII (AHF) and von Willebrand Factor (VWF).

ALPHANATE is prepared from pooled human plasma by cryoprecipitation of FVIII, fractional solubilization, and further purification employing heparin-coupled, cross-linked agarose which has an affinity to the heparin binding domain of VWF/FVIII:C complex. The product is treated with a mixture of tri-n-butyl phosphate (TNBP) and polysorbate 80 to inactivate enveloped viruses. The product is also subjected to an 80 °C heat treatment step for 72 hours to inactivate enveloped and non-enveloped viruses. However, no procedure has been shown to be totally effective in removing viral infectivity from coagulation factor products.

ALPHANATE is labeled with the antihemophilic factor potency (FVIII:C activity) in International Units (IU) FVIII/vial and with VWF:RCo activity expressed in IU VWF:RCo/vial. The activities are referenced to their respective international standards established by the World Health Organization. One IU of FVIII or one IU of VWF:RCo is approximately equal to the amount of FVIII or VWF:RCo activity in 1 mL of freshly-pooled human plasma.

ALPHANATE contains human albumin as a stabilizer, resulting in a final container concentrate with a specific activity of at least 5 FVIII:C IU/mg total protein. ALPHANATE contains no preservatives.

The composition of ALPHANATE after reconstitution is as follows:

Name of Ingredients | Nominal Composition |  |  |  |  | Units/Container
Factor VIII | 250 | 500 | 1000 | 1500 | 2000 | IU
von Willebrand Factor | > 400 | > 400 | > 400 | > 400 | > 400 | IU per 1000 IU Factor VIII
Albumin (Human) | 25 | 25 | 50 | 50 | 50 | mg
Arginine | 90 | 90 | 175 | 175 | 175 | mg
Histidine | 20 | 20 | 40 | 40 | 40 | mg
Water for Injectiona | 5 | 5 | 10 | 10 | 10 | mL
a Supplied in a separate diluent vial

Viral Reduction Capacity

The results of virus validation studies performed to determine virus reduction factors associated with several steps in the manufacturing process of ALPHANATE are summarized in Table 3.

In vitro inactivation studies to evaluate the solvent detergent treatment (0.3% Tri-n-butyl Phosphate and 1.0% Polysorbate 80) step in the manufacture of ALPHANATE were conducted to assess the capability of the step to inactivate enveloped viruses, such as Human Immunodeficiency viruses (HIV), as well as marker viruses such as Sindbis virus (SIN, a model for Hepatitis C virus), Vesicular Stomatitis virus (VSV, a model for large, enveloped RNA virus), Bovine Herpes virus (BHV, a model for Hepatitis B virus) and Bovine Viral Diarrhea virus (BVD, a model for Hepatitis C virus). In vitro inactivation studies to evaluate the dry heat treatment (80 °C, 72 hours) step in the manufacture of ALPHANATE were conducted to assess the capability of the step to inactivate both enveloped and non-enveloped viruses, such as Hepatitis A virus (HAV), human Poliovirus Sabin type 2 (POL, a model for HAV), Canine Parvovirus (CPV, a model for Parvovirus B19), BHV and BVD. Other steps in the manufacturing process of ALPHANATE (precipitation with 3.5% polyethylene glycol (PEG), heparin affinity chromatography and lyophilization) were also evaluated for virus elimination capability using several enveloped and non-enveloped viruses as shown in Table 3.

Table 3: Virus Log Reduction
Virus (Model Virus for) | 3.5% PEG Precipitation | Solvent- Detergent | Column Chromatography | Lyophilization | Dry Heat Cycle (80 °C, 72 hr) | Total Log Reduction
BHV (HBV) | < 1.0 | ≥ 8.0 | 7.6 | 1.3 | 2.1 | ≥ 19.0
BVD (HCV) | < 1.0 | ≥ 4.5 | < 1.0 | < 1.0 | ≥ 4.9 | ≥ 9.4
POL (HAV) | 3.3 | – | < 1.0 | 3.4 | ≥ 2.5 | ≥ 9.2
CPV (B19) | 1.2 | – | < 1.0 | < 1.0 | 4.1 | 5.3
VSV | – | ≥ 4.1 | – | – | – | ≥ 4.1
SIN (HCV) | – | ≥ 4.7 | – | – | – | ≥ 4.7
HIV–1 | < 1.0 | ≥ 11.1 | ≥ 2.0 | – | – | ≥ 13.1
HIV–2 | – | ≥ 6.1 | – | – | – | ≥ 6.1
HAV | – | – | – | 2.1 | ≥ 5.8 | ≥ 7.9

Additionally, the manufacturing process was investigated for its capacity to decrease infectivity of an experimental agent of transmissible spongiform encephalopathy (TSE), considered as a model for the vCJD and CJD agents.

Several of the individual production steps in ALPHANATE manufacturing process have been shown to decrease TSE infectivity of an experimental model agent.^11 TSE reduction steps include: 3.5% polyethylene glycol precipitation (3.23 log10), affinity chromatography (3.50 log10) and saline precipitation (1.36 log10). These studies provide reasonable assurance that low levels of CJD/vCJD agent infectivity, if present in the starting material, would be removed.

12 CLINICAL PHARMACOLOGY

12.1 Mechanism of Action

ALPHANATE contains antihemophilic factor (FVIII) and von Willebrand factor (VWF), constituents of normal plasma. FVIII is an essential cofactor in activation of factor X leading to formation of thrombin and fibrin. VWF promotes platelet aggregation and platelet adhesion on damaged vascular endothelium; it also serves as a stabilizing carrier protein for the procoagulant protein FVIII.^(12, 13)

After administration, ALPHANATE temporarily replaces the missing coagulation factor VIII and von Willebrand factor needed for effective hemostasis.

12.3 Pharmacokinetics

Pharmacokinetics in Hemophilia A

Following the administration of ALPHANATE during clinical trials, the mean in vivo half-life of FVIII observed in 12 adult subjects with severe hemophilia A was 17.9 ± 9.6 hours. In this same study, the in vivo recovery was 96.7 ± 14.5% at 10 minutes post-infusion. Recovery at 10 minutes post-infusion was also determined as 2.4 ± 0.4 IU FVIII rise/dL plasma per IU FVIII infused/kg body weight.

Pharmacokinetics in von Willebrand Disease (VWD)

A pharmacokinetic crossover study was conducted in 14 non-bleeding subjects with VWD (1 type 1, 2 type 2A, and 11 type 3) comparing the pharmacokinetics of ALPHANATE (A-SD/HT) and an earlier formulation, ALPHANATE (A-SD). Subjects received, in random order at least seven days apart, a single intravenous dose of each product, 60 IU VWF:RCo/kg (75 IU VWF:RCo/kg in subjects younger than 18 years of age). Pharmacokinetic parameters were similar for the two products and indicated that they were biochemically equivalent. Pharmacokinetic analysis of ALPHANATE (A-SD/HT) in the 14 subjects revealed the following results: the median plasma levels (% normal) of VWF:RCo rose from 10 IU/dL (range: 10 to 27 IU/dL) at baseline to 206 IU/dL (range: 87 to 440 IU/dL) 15 minutes post-infusion; median plasma levels of FVIII:C rose from 5 IU/dL (range: 2 to 114 IU/dL) to 206 IU/dL (range: 110 to 421 IU/dL). The median bleeding time (BT) prior to infusion was 30 minutes (mean, 28.8 ± 4.41 minutes; range: 13.5 to 30 minutes), which shortened to 10.38 minutes (mean, 10.4 ± 3.2 minutes; range: 6 to 16 minutes) 1 hour post-infusion.

Following infusion of ALPHANATE (A-SD/HT), the median half-lives for VWF:RCo, FVIII:C and VWF:Ag were 6.91 hours (range: 3.8 to 16.22 hours), 20.92 hours (range: 7.19 to 32.2 hours), and 12.8 hours (range: 10.34 to 17.45 hours), respectively. The median incremental in vivo recoveries of VWF:RCo and FVIII:C were 3.12 (IU/dL)/(IU/kg) [range: 1.28 to 5.73 (IU/dL)/(IU/kg)] for VWF:RCo and 1.95 (IU/dL)/(IU/kg) [range: 1.33 to 3.32 (IU/dL)/(IU/kg)] for FVIII:C.

The pharmacokinetic data in VWD are summarized in Table 4.

Table 4: Pharmacokinetic data in VWD
Parameter | Plasma VWF:RCo (Mean ± SD) | Plasma FVIII:C (Mean ± SD) | Plasma VWF:Ag (Mean ± SD)
Number of patients | 14 | 14 | 14
Mean plasma levels (IU/dL)
Baseline | 11.86 ± 4.97 | 21.00 ± 33.83 | –
15 minutes post-infusion | 215.50 ± 101.70 | 215.29 ± 94.26 | –
T½ (Half-life in hours) | 7.67 ± 3.32 | 21.58 ± 7.79 | 13.06 ± 2.20
Incremental in vivo recovery in (IU/dL)/(IU/kg) | 3.29 ± 1.46 | 2.13 ± 0.58 | –

Following infusion of both ALPHANATE (A-SD) and ALPHANATE (A-SD/HT), an increase in the size of VWF multimers was seen and persisted for at least 24 hours. The shortening of the BT was transient, lasting less than 6 hours following treatment and did not correlate with the presence of large and intermediate size VWF multimers.^14

14 CLINICAL STUDIES

In a prospective, multi-center clinical study, 37 subjects with VWD (6 Type 1, 19 Type 2, 12 Type 3) underwent 59 surgical procedures for which ALPHANATE (A-SD) or ALPHANATE (A-SD/HT) was administered [21 subjects received ALPHANATE (A-SD), 18 received ALPHANATE (A-SD/HT), and 2 received both products] for bleeding prophylaxis (see Table 5). An initial pre-operative infusion of 60 IU VWF:RCo/kg (75 IU VWF:RCo/kg for subjects less than 18 years of age), was administered one hour before surgery. A blood sample was obtained 15 minutes after the initial infusion for the determination of the plasma FVIII:C level. The level had to equal or exceed 100% of normal for an operation to proceed. No cryoprecipitate or alternative FVIII product was administered during these surgical procedures. Platelets were required in two subjects. The protocol permitted intra-operative infusions of ALPHANATE (A-SD) and ALPHANATE (A-SD/HT) at 60 IU VWF:RCo/kg (75 IU VWF:RCo/kg for subjects less than 18 years of age) to be administered as required according to the judgment of the investigator.

Table 5: Number of and Types of Surgical Procedures
Parameter | Treatment with Alphanate |  | Total
Type of Surgical Procedure | A-SD | A-SD/HT | Total
Number of Subjects | 21 | 18 | 37^
Dental | 14 | 6 | 20
Dermatologic | 1 | 1 | 2
Gastrointestinal | 4 | 4 | 8
Gastrointestinal (diagnostic) | 6 | 0 | 6
Genitourinary | 0 | 2 | 2
Gynecologic | 2 | 1 | 3
Head and neck | 1 | 1 | 2
Orthopedic | 4 | 3 | 7
Vascular | 3 | 6 | 9
Total number of procedures | 35 | 24 | 59
^ Two subjects received both preparations; the total number of subjects is therefore less than the sum of the columns.

Post-operative infusions at doses of 40 to 60 IU VWF:RCo/kg (50 to 75 IU VWF:RCo/kg for pediatric subjects) were administered at 8 to 12-hour intervals until healing had occurred. For maintenance of secondary hemostasis (after primary hemostasis was achieved), the dose was reduced after the third post-operative day [see Dosage and Administration (2.2)].

Overall, in the surgical procedures using either product, the BT at 30 minutes post-infusion was fully corrected in 18 (32.7%) cases, partially corrected in 24 (43.6%) cases, not corrected in 12 (21.8%) cases, and was not done in one case (1.8%). Overall, the mean blood loss was lower than predicted prospectively.

Surgical infusion summary data are included in Table 6.

Table 6: Prophylaxis with ALPHANATE (A-SD) and/or ALPHANATE (A-SD/HT) in Surgery
Parameter | A-SD | A-SD/HT | Total
Number of patients | 21 | 18 | 37*
Number of surgical procedures | 35 | 24 | 59
Median number of infusions per surgical procedure (range) | 3 (1-13) | 4 (1 – 18) | 4 (1-18)
Median dosage IU VWF:RCo/kg
Infusion #1 (range) | 59.8 (19.8-75.1) | 59.9 (40.6 – 75.0) | 59.9 (19.8-75.1)
Infusion ≥ #2 combined (range) | 40.0 (4.5-75.1) | 40.0 (10.0 – 63.1) | 40.0 (4.5-75.1)
* Two subjects received both products

Additionally, surgical procedures using ALPHANATE SD/HT only were categorized as major, minor or invasive procedures according to definitions used in the study. The outcome of each surgery was evaluated according to a clinical rating scale (excellent, good, poor or none) and was considered successful if the outcome was excellent or good.

Study results also were evaluated independently by two referees with clinical experience in this field in the same way (surgery categorization and outcome of each surgery according to a clinical rating scale). There was a high level of agreement between the referee evaluations and the analyzed outcome data, with a decrease of only a single success in achieving hemostasis (21/24 [referees evaluation] vs. 22/24 [investigators evaluation]).

A retrospective, multi-center study was performed to assess the efficacy of ALPHANATE (A-SD/HT) as replacement therapy in preventing excessive bleeding in subjects with congenital VWD undergoing surgical or invasive procedures, for whom DDAVP was ineffective or inadequate. A total of 61 surgeries/procedures in 39 subjects were evaluated.^15

Of the 39 subjects, 18 had Type 1 VWD (46.2%); 12 subjects (30.8%) had Type 2 VWD, and 9 subjects (23.1%) had Type 3 VWD. Median age was 40 years; approximately one-half of the subjects were male.

The primary efficacy variable was the overall treatment outcome for each surgical or invasive procedure, as rated by the investigator using a 4-point verbal rating scale (VRS): “excellent,” “good,” “poor,” or “none (no indication of efficacy).” The categorization of the replacement treatment outcome was based upon the investigator’s clinical experience and defined in Table 7.

Table 7: Rating Scale and Clinical Efficacy of ALPHANATE Therapy
Rating | Clinical Efficacy*
Rating | Hemostasis | Dosing
Excellent | Hemostasis not different from that expected for subjects without known bleeding disorders. | No upward dosage adjustment for ALPHANATE replacement therapy.
Good | Hemostasis slightly inferior from that expected for subjects without known bleeding disorders but judged as not clinically relevant. | Minor upward dosage adjustment for ALPHANATE replacement therapy.
Poor | Less hemostasis than expected for subjects without known bleeding disorders attributed to vWD despite ALPHANATE replacement therapy. | Relevant upward dosage adjustment for ALPHANATE replacement therapy. No need for alternative therapy.
None | Severe bleeding attributed to vWD despite ALPHANATE replacement therapy. | Relevant upward dosage adjustment for ALPHANATE replacement therapy and/or need for alternative unexpected therapy.
* The efficacy assessment period included the entire perioperative period.

In addition, an independent referee committee was convened to evaluate the efficacy outcomes. More than 90% of the surgical outcomes received an investigator and referee’s overall and daily rating of “effective” (“excellent” or “good”) in achieving hemostasis/preventing bleeding.

The majority of ratings were considered “excellent” (≥ 81.3% in each VWD type). Nine Type 3 subjects underwent 1 major and 15 minor procedures. Two procedures (1 major and 1 minor) in 1 subject with Type 3 VWD received an overall efficacy rating of “none,” and one minor procedure in a subject with Type 2 VWD received an overall efficacy rating of “poor.”

15 REFERENCES

1. Srivastava, A., Brewer, A.K., et al. WFH Guidelines: Guidelines for the management of hemophilia. Haemophilia 2013; 19, e1-e47.
2. Kempton, C.L., White, G.C. How we treat a hemophilia A patient with a factor VIII inhibitor. Blood 2009; 113:11-17.
3. Federici, A.B., Baudo, F., Caracciolo, C., Mancuso, G., Mazzucconi, M.G., Musso, R., Schinco, P.C., Targhetta. R., Mannucci, P.M. Clinical efficacy of highly purified, doubly virus-inactivated factor VIII/von Willebrand factor concentrate (Fanhdi) in the treatment of von Willebrand disease: a retrospective clinical study. Haemophilia 2002; 8:761-767.
4. Federici, A.B. Management of von Willebrand disease with factor VIII/von Willebrand factor concentrates: results from current studies and surveys. Blood Coagul Fibrinolysis 2005; 16(Suppl 1):S17-S21.
5. Mannucci, P.M. How I treat patients with von Willebrand disease. Blood 2001; 97:1915-1919.
6. Mannucci, P.M. Treatment of von Willebrand’s Disease. N Engl J Med 2004; 351:47-58.
7. Nichols, W.L. et al.; NHLBI VWD Expert Panel. The Diagnosis, Evaluation, and Management of von Willebrand Disease. US Department of Health and Human Services, National Institutes of Health, National Heart, Lung, and Blood Institute 2007; NIH No. 08-5832.
8. Mannucci, P.M., Franchini, M., Castaman, G., Federici, A.B.; Italian Association of Haemophilia Centres. Evidence-based recommendations on the treatment of von Willebrand disease in Italy. Blood Transfus 2009; 7:117-126.
9. Coppola, A., Franchini, M., Makris M. Santagostino, E. Minno, G.DI, Mannucci, P.M. Thrombotic adverse events to coagulation factor concentrates for treatment of patients with haemophilia and von Willebrand disease: a systematic review of prospective studies. Haemophilia 2012; 18, e173-e187.
10. Soni, N.S., Patel A.R., Vohra, R.M., Shah P.C. Hemophiliac with Hemolytic Anemia resulting from Factor VIII Concentrate. Acta Haemato 1977; 58:294-297.
11. Diez, J.M., Caballero, S., Belda, P., Otegui, M., Gajardo, R., Jorquera, J.I. Elimination capacity of a TSE-model agent in the manufacturing process of Alphanate/Fanhdi, a human factor VIII/VWF complex concentrate. Haemophilia 2009; 15(6):1249-1257.
12. Hoyer, L.W. The Factor VIII Complex: Structure and Function. Blood 1981; 58:1-13.
13. Meyer, D., Girma, J-P. von Willebrand Factor: Structure and Function. Thrombosis and Haemostasis 1993; 70:99-104.
14. Mannucci, P.M., Chediak, J., Hanna, W. Byrnes, J.J., Kessler, C.M, Ledford, M., Retzios, A.D., Kapelan, B.A., Gallagher, P., Schwartz, R.S., and the Alphanate Study Group. Treatment of von Willebrand’s Disease (VWD) with a high purity factor VIII concentrate: Dissociation between correction of the bleeding time (BT), VWF multimer pattern, and treatment efficacy. Blood 1999; 94 (Suppl 1, Part 2 of 2):98b.
15. Rivard, G.E., Aledort, L., et al. Efficacy of factor VIII/von Willebrand factor concentrate Alphanate in preventing excessive bleeding during surgery in subjects with von Willebrand disease. Haemophilia 2008; 14, 271-275.

16 HOW SUPPLIED/STORAGE AND HANDLING

How Supplied

ALPHANATE is supplied in sterile, lyophilized form in a single dose vial with a vial of diluent (Sterile Water for Injection, USP) and a Mix2Vial filter transfer set. IU activity of FVIII and VWF:RCo are stated on the carton and label of each vial.

ALPHANATE is available in the following potencies and color coded based upon assay on the carton and label as follows:

Potency | NDC | Assay Color Code
250 IU FVIII/5 mL single dose vial | 68516-4611-1 or 68516-4616-1 | 250 IU FVIII Range – gray box
500 IU FVIII/5 mL single dose vial | 68516-4612-1 or 68516-4617-1 | 500 IU FVIII Range - green box
1000 IU FVIII/10 mL single dose vial | 68516-4613-2 or 68516-4618-2 | 1000 IU FVIII Range – blue box
1500 IU FVIII/10 mL single dose vial | 68516-4614-2 or 68516-4619-2 | 1500 IU FVIII Range – orange box
2000 IU FVIII/10 mL single dose vial | 68516-4615-2 or 68516-4620-2 | 2000 IU FVIII Range - magenta box

Storage and Handling

ALPHANATE is stable for three years, up to the expiration date printed on its label, provided that the storage temperature does not exceed 25 °C (77 °F). Do not freeze.

17 PATIENT COUNSELING INFORMATION

Advise the patient:

- To contact their healthcare provider or go to the emergency department right away if a hypersensitivity reaction occurs. Early signs of hypersensitivity reactions may include rash, hives, itching, facial swelling, tightness of the chest, and wheezing [see Warnings and Precautions (5.1)].
- To contact their physician or treatment center for further treatment and/or assessment if they experience a lack of clinical response to factor VIII replacement therapy, as this may be a manifestation of an inhibitor [see Warnings and Precautions (5.2)].
- To contact their healthcare provider or go to the emergency department right away if a thromboembolic event should occur [see Warnings and Precautions (5.3)].
- That despite stringent procedures designed to reduce risk, the risk of transmitting infectious agents cannot be totally eliminated. Advise patients, especially pregnant women and immunocompromised individuals, to report any signs and symptoms of fever, rash, joint pain, or sore throat, to their physician immediately [see Warnings and Precautions (5.6)].

Manufactured by:
Grifols Biologicals LLC
5555 Valley Boulevard
Los Angeles, CA 90032, U.S.A.
U. S. License No. 1694

3063713

Principal Display Panel – 250 IU Vial Label

NDC 68516-4605-1 250 IU FVIII Range

Antihemophilic Factor/
von Willebrand Factor
Complex (Human)
Alphanate® 5 mL

Solvent Detergent / Heat Treated

Storage: Store at temperatures
not exceeding 25 °C (77 °F).
Rx only. Single dose container for
intravenous administration only.
GRIFOLS U.S. License No. 1694
Instructions: Reconstitute
with 5 mL of Sterile Water
for Injection, USP. Administer
promptly after reconstitution
and do not refrigerate. Discard
unused contents. For information
on dosage and directions for
administration, see accompanying
pamphlet. Contains no
preservatives. The patient and
physician should discuss the risks
and benefits of this product.
Grifols Biologicals LLC
5555 Valley Boulevard
Los Angeles, CA 90032, U.S.A.
Lot
EXP
IU FVIII/Vial
IU VWF:RCo/Vial 3063712
Lot
IU FVIII/Vial
IU VWF:RCo/Vial
Alphanate® 5 mL NDC 68516-4605-1

Principal Display Panel – 250 IU Carton Label
NDC 68516-4616-1 250 IU FVIII Range
Antihemophilic Factor/von Willebrand
Factor Complex (Human)
Alphanate®
Solvent Detergent / Heat Treated
Rx only
For Intravenous Administration 5 mL
GRIFOLS
Contents: One vial Antihemophilic Factor/von Willebrand
Factor Complex (Human), Alphanate®, one vial
5 mL Sterile Water for Injection, USP, one
Mix2Vial® filter transfer set, and directions for use.
Composition:
Factor VIII, von Willebrand Factor, Arginine, Albumin
and Histidine.
Contains no preservatives.
Administer within three hours of reconstitution.
Discard unused content.
GRIFOLS
Warning:
This product is prepared from large pools of
human plasma. Human blood and its components
may transmit infectious agents. See package
insert, WARNINGS AND PRECAUTIONS.
Instructions: The patient and physician should
discuss the risks and benefits of this product.
For information on dosage and directions for
administration, see enclosed package insert.
Storage: Store at temperatures not exceeding
25 °C (77 °F). Do not freeze.
Single dose container for intravenous
administration only.
Grifols Biologicals LLC
5555 Valley Boulevard
Los Angeles, CA 90032, USA
U.S. License No. 1694
GRIFOLS
3063711
GTIN 00368516461617
LOT XXXXXXXXXX
EXP DDMMMYYYY
SN XXXXXXXXXX XXXXXX
IU FVIII/Vial XXXX
IU VWF: RCo/Vial XXXX

Principal Display Panel – 500 IU Vial Label
NDC 68516-4606-1 500 IU FVIII Range
Antihemophilic Factor/
von Willebrand Factor
Complex (Human)
Alphanate® 5 mL

Solvent Detergent / Heat Treated
Storage: Store at temperatures
not exceeding 25 °C (77 °F).
Rx only. Single dose container for
intravenous administration only.
GRIFOLS U.S. License No. 1694
Instructions: Reconstitute
with 5 mL of Sterile Water
for Injection, USP. Administer
promptly after reconstitution
and do not refrigerate. Discard
unused contents. For information
on dosage and directions for
administration, see accompanying
pamphlet. Contains no
preservatives. The patient and
physician should discuss the risks
and benefits of this product.
Grifols Biologicals LLC
5555 Valley Boulevard
Los Angeles, CA 90032, U.S.A.
Lot
EXP
IU FVIII/Vial
IU VWF:RCo/Vial 3063710
Lot
IU FVIII/Vial
IU VWF:RCo/Vial
Alphanate® 5 mL NDC 68516-4606-1

Principal Display Panel – 500 IU Carton Label
NDC 68516-4617-1 500 IU FVIII Range
Antihemophilic Factor/von Willebrand
Factor Complex (Human)
Alphanate®
Solvent Detergent / Heat Treated
Rx only
For Intravenous Administration 5 mL
GRIFOLS
Contents:
One vial Antihemophilic Factor/von Willebrand
Factor Complex (Human), Alphanate®, one vial
5 mL Sterile Water for Injection, USP, one
Mix2Vial® filter transfer set, and directions for use.
Composition:
Factor VIII, von Willebrand Factor, Arginine, Albumin
and Histidine.
Contains no preservatives.
Administer within three hours of reconstitution.
Discard unused contents.
GRIFOLS
Warning:
This product is prepared from large pools of
human plasma. Human blood and its components
may transmit infectious agents. See package
insert, WARNINGS AND PRECAUTIONS.
Instructions: The patient and physician should
discuss the risks and benefits of this product.
For information on dosage and directions for
administration, see enclosed package insert.
Storage: Store at temperatures not exceeding
25 °C (77 °F). Do not freeze.
Single dose container for intravenous
administration only.
Grifols Biologicals LLC
5555 Valley Boulevard
Los Angeles, CA 90032, USA
U.S. License No. 1694
GRIFOLS
3063709
GTIN 00368516461716
LOT XXXXXXXXXX
EXP DDMMMYYYY
SN XXXXXXXXXX XXXXXX
IU FVIII/Vial XXXX
IU VWF: RCo/Vial XXXX

Principal Display Panel – 1000 IU Vial Label

NDC 68516-4607-2 1000 IU FVIII Range

Antihemophilic Factor/
von Willebrand Factor
Complex (Human)
Alphanate® 10 mL

Solvent Detergent / Heat Treated
Storage: Store at temperatures
not exceeding 25 °C (77 °F).
Rx only. Single dose container for
intravenous administration only.
GRIFOLS U.S. License No. 1694
Instructions: Reconstitute
with 10 mL of Sterile Water
for Injection, USP. Administer
promptly after reconstitution
and do not refrigerate. Discard
unused contents. For information
on dosage and directions for
administration, see accompanying
pamphlet. Contains no
preservatives. The patient and
physician should discuss the risks
and benefits of this product.
Grifols Biologicals LLC
5555 Valley Boulevard
Los Angeles, CA 90032, U.S.A.
Lot
EXP
IU FVIII/Vial
IU VWF:RCo/Vial 3063708
Lot
IU FVIII/Vial
IU VWF:RCo/Vial
Alphanate® 10 mL NDC 68516-4607-2

Principal Display Panel – 1000 IU Carton Label
NDC 68516-4618-2 1000 IU FVIII Range
Antihemophilic Factor/von Willebrand
Factor Complex (Human)
Alphanate®
Solvent Detergent / Heat Treated
Rx only
For Intravenous Administration 10 mL
GRIFOLS
Contents:
One vial Antihemophilic Factor/von Willebrand
Factor Complex (Human), Alphanate®, one vial
10 mL Sterile Water for Injection, USP, one
Mix2Vial® filter transfer set, and directions for use.
Composition:
Factor VIII, von Willebrand Factor, Arginine, Albumin
and Histidine.
Contains no preservatives.
Administer within three hours of reconstitution.
Discard unused contents.
GRIFOLS
Warning:
This product is prepared from large pools of
human plasma. Human blood and its components
may transmit infectious agents. See package
insert, WARNINGS AND PRECAUTIONS.
Instructions: The patient and physician should
discuss the risks and benefits of this product.
For information on dosage and directions for
administration, see enclosed package insert.
Storage: Store at temperatures not exceeding
25 °C (77 °F). Do not freeze.
Single dose container for intravenous
administration only.
Grifols Biologicals LLC
5555 Valley Boulevard
Los Angeles, CA 90032, USA
U.S. License No. 1694
GRIFOLS
3063707
GTIN 00368516461822
LOT XXXXXXXXXX
EXP DDMMMYYYY
SN XXXXXXXXXX XXXXXX
IU FVIII/Vial XXXX
IU VWF: RCo/Vial XXXX

Principal Display Panel – 1500 IU Vial Label

NDC 68516-4608-2 1500 IU FVIII Range

Antihemophilic Factor/
von Willebrand Factor
Complex (Human)
Alphanate® 10 mL

Solvent Detergent / Heat Treated
Storage: Store at temperatures
not exceeding 25 °C (77 °F).
Rx only. Single dose container for
intravenous administration only.
GRIFOLS U.S. License No. 1694
Instructions: Reconstitute
with 10 mL of Sterile Water
for Injection, USP. Administer
promptly after reconstitution
and do not refrigerate. Discard
unused contents. For information
on dosage and directions for
administration, see accompanying
pamphlet. Contains no
preservatives. The patient and
physician should discuss the risks
and benefits of this product.
Grifols Biologicals LLC
5555 Valley Boulevard
Los Angeles, CA 90032, U.S.A.
Lot
EXP
IU FVIII/Vial
IU VWF:RCo/Vial 3063706
Lot
IU FVIII/Vial
IU VWF:RCo/Vial
Alphanate®10 mL NDC 68516-4608-2

Principal Display Panel – 1500 IU Carton Label
NDC 68516-4619-2 1500 IU FVIII Range
Antihemophilic Factor/von Willebrand
Factor Complex (Human)
Alphanate®
Solvent Detergent / Heat Treated
Rx only
For Intravenous Administration 10 mL
GRIFOLS
Contents:
One vial Antihemophilic Factor/von Willebrand
Factor Complex (Human), Alphanate®, one vial
10 mL Sterile Water for Injection, USP, one
Mix2Vial® filter transfer set, and directions for use.
Composition:
Factor VIII, von Willebrand Factor, Arginine, Albumin
and Histidine.
Contains no preservatives.
Administer within three hours of reconstitution.
Discard unused contents.
GRIFOLS
Warning:
This product is prepared from large pools of
human plasma. Human blood and its components
may transmit infectious agents. See package
insert, WARNINGS AND PRECAUTIONS.
Instructions: The patient and physician should
discuss the risks and benefits of this product.
For information on dosage and directions for
administration, see enclosed package insert.
Storage: Store at temperatures not exceeding
25 °C (77 °F). Do not freeze.
Single dose container for intravenous
administration only.
Grifols Biologicals LLC
5555 Valley Boulevard
Los Angeles, CA 90032, USA
U.S. License No. 1694
GRIFOLS
3063705
GTIN 00368516461921
LOT XXXXXXXXXX
EXP DDMMMYYYY
SN XXXXXXXXXX XXXXXX
IU FVIII/Vial XXXX
IU VWF: RCo/Vial XXXX

Principal Display Panel – 2000 IU Vial Label

NDC 68516-4610-2 2000 IU FVIII Range

Antihemophilic Factor/
von Willebrand Factor
Complex (Human)
Alphanate® 10 mL

Solvent Detergent / Heat Treated
Storage: Store at temperatures
not exceeding 25 °C (77 °F).
Rx only. Single dose container for
intravenous administration only.
GRIFOLS U.S. License No. 1694
Instructions: Reconstitute
with 10 mL of Sterile Water
for Injection, USP. Administer
promptly after reconstitution
and do not refrigerate. Discard
unused contents. For information
on dosage and directions for
administration, see accompanying
pamphlet. Contains no
preservatives. The patient and
physician should discuss the risks
and benefits of this product.
Grifols Biologicals LLC
5555 Valley Boulevard
Los Angeles, CA 90032, U.S.A.
Lot
EXP
IU FVIII/Vial
IU VWF:RCo/Vial 3063704
Lot
10
IU FVIII/Vial
IU VWF:RCo/Vial
Alphanate®10 mL NDC 68516-4608-2

Principal Display Panel – 2000 IU Carton Label
NDC 68516-4620-2 2000 IU FVIII Range
Antihemophilic Factor/von Willebrand
Factor Complex (Human)
Alphanate®
Solvent Detergent / Heat Treated
Rx only
For Intravenous Administration 10 mL
GRIFOLS
Contents:
One vial Antihemophilic Factor/von Willebrand
Factor Complex (Human), Alphanate®, one vial
10 mL Sterile Water for Injection, USP, one
Mix2Vial® filter transfer set, and directions for use.
Composition:
Factor VIII, von Willebrand Factor, Arginine, Albumin
and Histidine.
Contains no preservatives.
Administer within three hours of reconstitution.
Discard unused contents.
GRIFOLS
Warning:
This product is prepared from large pools of
human plasma. Human blood and its components
may transmit infectious agents. See package
insert, WARNINGS AND PRECAUTIONS.
Instructions: The patient and physician should
discuss the risks and benefits of this product.
For information on dosage and directions for
administration, see enclosed package insert.
Storage: Store at temperatures not exceeding
25 °C (77 °F). Do not freeze.
Single dose container for intravenous
administration only.
Grifols Biologicals LLC
5555 Valley Boulevard
Los Angeles, CA 90032, USA
U.S. License No. 1694
GRIFOLS
3063703
GTIN 00368516462027
LOT XXXXXXXXXX
EXP DDMMMYYYY
SN XXXXXXXXXX XXXXXX
IU FVIII/Vial XXXX
IU VWF: RCo/Vial XXXX

Principal Display Panel – 5 mL Vial Label
NDC 76297-002-02
Sterile Water for Injection, USP
5 mL
Rx only
3057422
For reconstitution of accompanying product
Single-Dose Container, Nonpyrogenic
Do not use unless clear. No antimicrobial agent or other substance has been added. Do not use for intravascular injection without making approximately isotonic by addition of suitable solute. Discard unused portion.
Mfd by: Laboratorios Grifols, S.A. Parets del Vallès,
Barcelona 08150 Spain
Lot
EXP

Principal Display Panel – 10 mL Vial Label
NDC 76297-002-12
Sterile Water for Injection, USP
10 mL
Rx only
3057423
For reconstitution of accompanying product
Single-Dose Container, Nonpyrogenic
Do not use unless clear. No antimicrobial agent or other substance has been added. Do not use for intravascular injection without making approximately isotonic by addition of suitable solute. Discard unused portion.
Mfd by: Laboratorios Grifols, S.A. Parets del Vallès,
Barcelona 08150 Spain
Lot
EXP